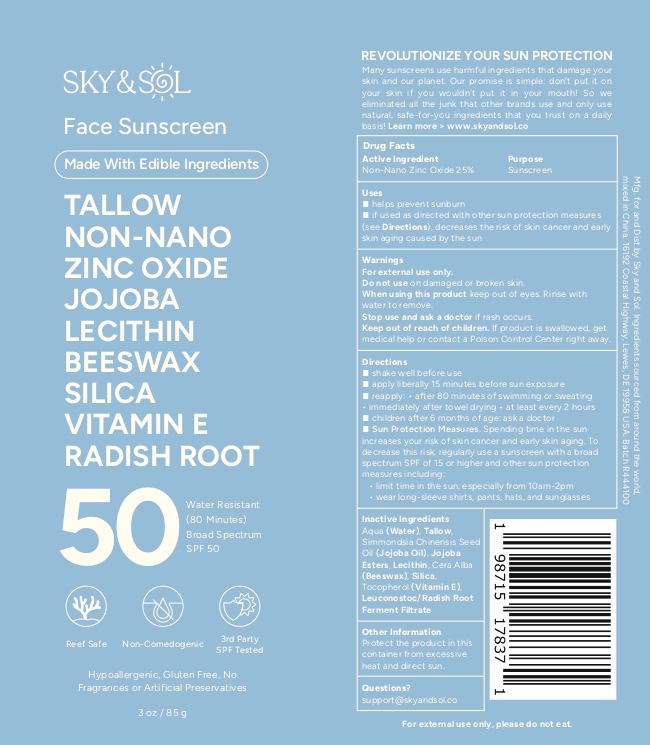 DRUG LABEL: Sky and Sol Face Sunscreen SPF 50
NDC: 84632-5050 | Form: CREAM
Manufacturer: Delta Ecommerce LLC
Category: otc | Type: HUMAN OTC DRUG LABEL
Date: 20260201

ACTIVE INGREDIENTS: ZINC OXIDE 25 g/100 g
INACTIVE INGREDIENTS: JOJOBA OIL; ASTAXANTHIN; BEESWAX; HYDROLYZED JOJOBA ESTERS; LEUCONOSTOC/RADISH ROOT FERMENT FILTRATE; TALLOW; TAPIOCA STARCH; LECITHIN, SUNFLOWER; PINUS STROBUS BARK; AQUA

PURPOSE

Sunscreen

INDICATIONS AND USAGE

helps prevent sunburn, if used as directed with other sun protection measures
(see Directions), decreases the risk of skin cancer and early
skin aging caused by the sun

DOSAGE AND ADMINISTRATION

helps prevent sunburn
◼ if used as directed with other sun protection measures
(see Directions), decreases the risk of skin cancer and early
skin aging caused by the sun

WARNINGS

For external use only.
Do not use on damaged or broken skin.
When using this product keep out of eyes. Rinse with
water to remove.
Stop use and ask a doctor if rash occurs.

Keep out of reach of children. If product is swallowed, get
medical help or contact a Poison Control Center right away.

INACTIVE INGREDIENT

Aqua (Water), Tallow,
Simmondsia Chinensis Seed
Oil (Jojoba Oil), Jojoba
Esters, Lecithin, Cera Alba
(Beeswax), Silica,
Tocopherol (Vitamin E),
Leuconostoc/Radish Root
Ferment Filtrate